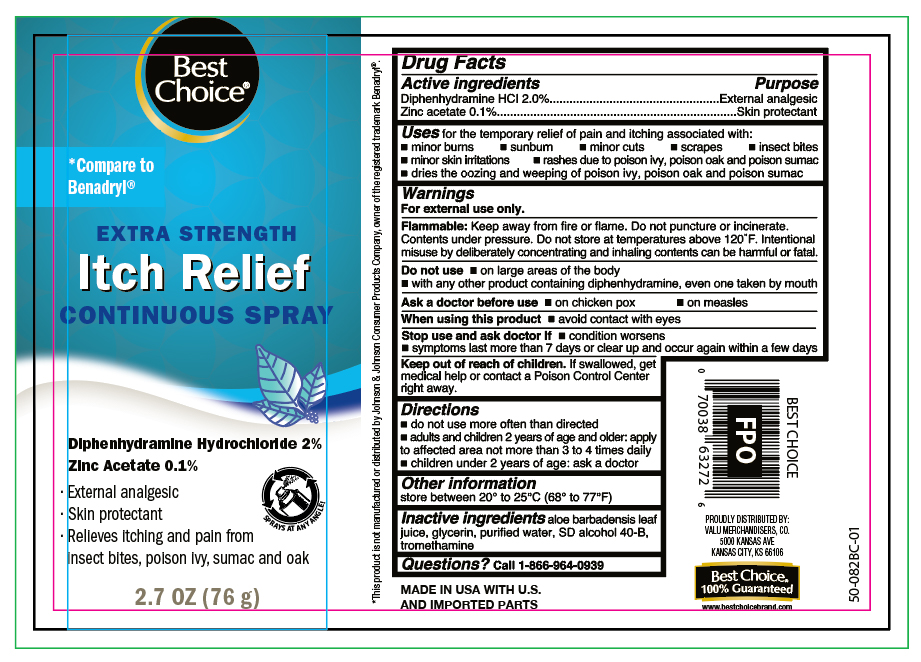 DRUG LABEL: Diphenhydramine HCl and Zinc Acetate
NDC: 63941-549 | Form: SPRAY
Manufacturer: VALU MERCHANDISERS, CO
Category: otc | Type: HUMAN OTC DRUG LABEL
Date: 20251124

ACTIVE INGREDIENTS: DIPHENHYDRAMINE HYDROCHLORIDE 1.52 g/88 mL; ZINC ACETATE 0.076 g/88 mL
INACTIVE INGREDIENTS: ALCOHOL; TROMETHAMINE; ALOE VERA LEAF; WATER; GLYCERIN

Best Choice Itch Relief Continuous Spray

Active ingredients

Diphenhydramine HCl 2.0%
Zinc Acetate 0.1%

Purpose

- External Analgesic
- Skin protectant

Uses

for temporary relief of pain and itching associated with:

- minor burns
- sunburns
- minor cuts
- scrapes
- insect bites
- minor skin irritations
- rashes due to poison ivy, poison oak and poison sumac
- dries the oozing and weeping of poison ivy, poison oak and poison sumac

Warnings

For external use only.

Flammable:

Keep away from fire or flame. Do not puncture or incinerate. Contents under pressure. Do not store at temperature above 120ºF. Intentional misuse by deliberately concentrating and inhaling contents cans be harmful or fatal.

Do not use

- on large areas of the body
- with any other products containing diphenhydramine, even one taken by mouth

Ask a doctor before use

- on chicken pox
- on measles

Stop use and ask doctor if

- condition worsens
- symptoms last more than 7 days or clear up and occur again within a few days

When using this product

- avoid contact with eyes
- use only as directed

Keep out of reach of children.

If swallowed, get medical help or contact a Poison Control Center right away.

Directions

- adults and children 2 years of age and older: apply to affected area not more than 3 to 4 times daily
- children under 2 years of age: ask a doctor

Other information

store between 20° to 25°C (68° to 77°F)

Inactive ingredients

aloe barbadensis leaf juice, glycerin, purified water, SD alcohol 40-B, tromethamine

Questions?

call 1-866-964-0939

Principal Display Panel

Best Choice

EXTRA STRENGTH

ITCH RELIEF

CONTINUOUS SPRAY

Diphenhydramine Hydrochloride 2%

Zinc Acetate 0.1%

- External analgesic
- Skin protectant
- Relieves Itching & pain from insect bites, poiuson ivy, sumac and oak

NET WT 2.7OZ (76 g)